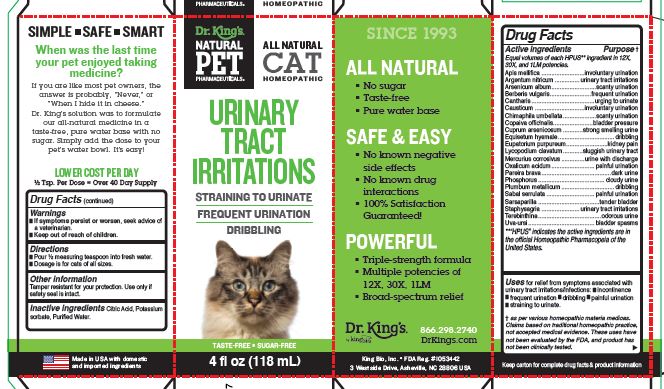 DRUG LABEL: Urinary Tract Irritations
NDC: 57955-4702 | Form: LIQUID
Manufacturer: King Bio Inc.
Category: homeopathic | Type: OTC ANIMAL DRUG LABEL
Date: 20221205

ACTIVE INGREDIENTS: APIS MELLIFERA 12 [hp_X]/118 mL; SILVER NITRATE 12 [hp_X]/118 mL; ARSENIC TRIOXIDE 12 [hp_X]/118 mL; BERBERIS VULGARIS ROOT BARK 12 [hp_X]/118 mL; LYTTA VESICATORIA 12 [hp_X]/118 mL; CAUSTICUM 12 [hp_X]/118 mL; CHIMAPHILA UMBELLATA WHOLE 12 [hp_X]/118 mL; COPAIFERA OFFICINALIS RESIN 12 [hp_X]/118 mL; CUPRIC ARSENITE 12 [hp_X]/118 mL; EQUISETUM HYEMALE WHOLE 12 [hp_X]/118 mL; EUTROCHIUM PURPUREUM ROOT 12 [hp_X]/118 mL; LYCOPODIUM CLAVATUM SPORE 12 [hp_X]/118 mL; MERCURIC CHLORIDE 12 [hp_X]/118 mL; OXALIC ACID DIHYDRATE 12 [hp_X]/118 mL; CHONDRODENDRON TOMENTOSUM ROOT 12 [hp_X]/118 mL; PHOSPHORUS 12 [hp_X]/118 mL; LEAD 12 [hp_X]/118 mL; SAW PALMETTO 12 [hp_X]/118 mL; SMILAX ORNATA ROOT 12 [hp_X]/118 mL; DELPHINIUM STAPHISAGRIA SEED 12 [hp_X]/118 mL; TURPENTINE OIL 12 [hp_X]/118 mL; ARCTOSTAPHYLOS UVA-URSI LEAF 12 [hp_X]/118 mL
INACTIVE INGREDIENTS: CITRIC ACID MONOHYDRATE; POTASSIUM SORBATE; WATER

Urinary Tract Irritations

Warnings

If symptoms persist or worsen, seek advice of
a veterinarian.

Keep out of reach of children.

Reference image:Urinary Tract .jpg

Directions

Pour ½ measuring teaspoon into fresh water.

Dosage is for cats of all sizes.

Reference image:Urinary Tract .jpg

Other information

Tamper resistant for your protection.

Use only if safety seal is intact.

This product has not been clinically tested.

Questions? Call 866.298.2740

King Bio, Inc. 3 Westside Drive

Asheville, NC 2806 USA

FDA Reg. #1053442

For latest product information and instructions: www.DrKings.com

Reference image:Urinary Tract .jpg

Keep out of reach of children.

Reference image:Urinary Tract .jpg

Ingredients

Equal volumes of each HPUS** ingredient in 12X,
30X, and 1LM potencies.

Apis mellifica, Argentum nitricum, Arsenicum album, Berberis vulgaris, Cantharis, Causticum, Chimaphila umbellata, Copaiva officinalis,Cuprum arsenicosum, Equisetum hyemale, Eupatorium purpureum, Lycopodium clavatum, Mercurius corrosivus, Oxalicum acidum, Pareira brava,
Phosphorus, Plumbum metallicum, Sabal serrulata, Sarsaparilla, Staphysagria, Terebinthina, Uva-ursi.

**“HPUS” indicates the active ingredients are in the official Homeopathic Pharmacopeia of the United States.

Reference image:Urinary Tract .jpg

Uses

For relief from symptoms associated with
urinary tract irritations/infections:

Incontinence

Frequent urination

Dribbling

Painful urination

Straining to urinate

† as per various homeopathic materia medicas.
Claims based on traditional homeopathic practice,
not accepted medical evidence. These uses have
not been evaluated by the FDA, and product has
not been clinically tested

Reference image:Urinary Tract .jpg

Inactive ingredients

Citric Acid, Potassium sorbate, and Purified Water.

Reference image:Urinary Tract .jpg

Active ingredients Purpose †
Equal volumes of each HPUS** ingredient in 12X,
30X, and 1LM potencies.
Apis mellifica ..........................involuntary urination
Argentum nitricum ............... urinary tract irritations
Arsenicum album............................scanty urination
Berberis vulgaris...........................frequent urination
Cantharis ......................................urging to urinate
Causticum ................................involuntary urination
Chimaphila umbellata........................scanty urination
Copaiva officinalis............................bladder pressure
Cuprum arsenicosum .................strong smelling urine
Equisetum hyemale.................................... dribbling
Eupatorium purpureum............................kidney pain
Lycopodium clavatum.................sluggish urinary tract
Mercurius corrosivus ...................urine with discharge
Oxalicum acidum............................. painful urination
Pareira brava............................................dark urine
Phosphorus .......................................... cloudy urine
Plumbum metallicum .................................. dribbling
Sabal serrulata ............................... painful urination
Sarsaparilla .......................................tender bladder
Staphysagria .......................... urinary tract irritations
Terebinthina.........................................odorous urine
Uva-ursi ...........................................bladder spasms

**“HPUS” indicates the active ingredients are in
the official Homeopathic Pharmacopeia of the
United States.

Reference image:Urinary Tract .jpg